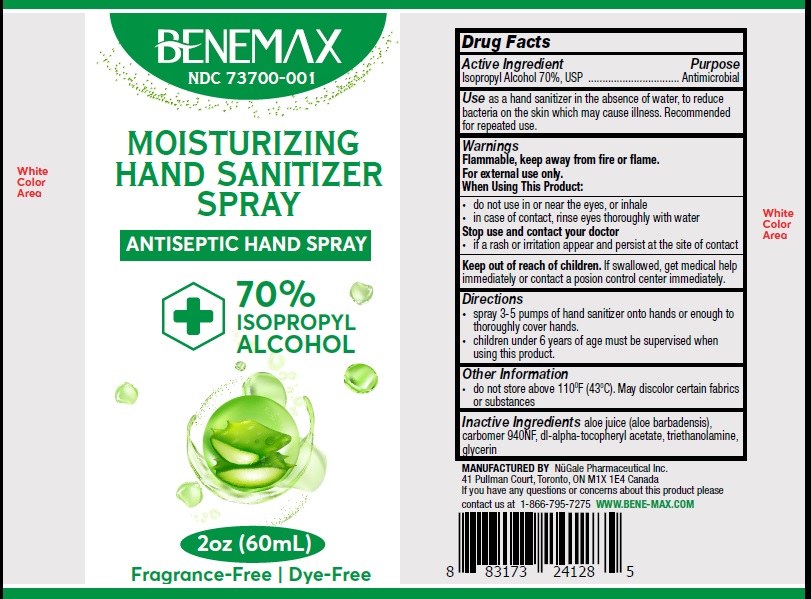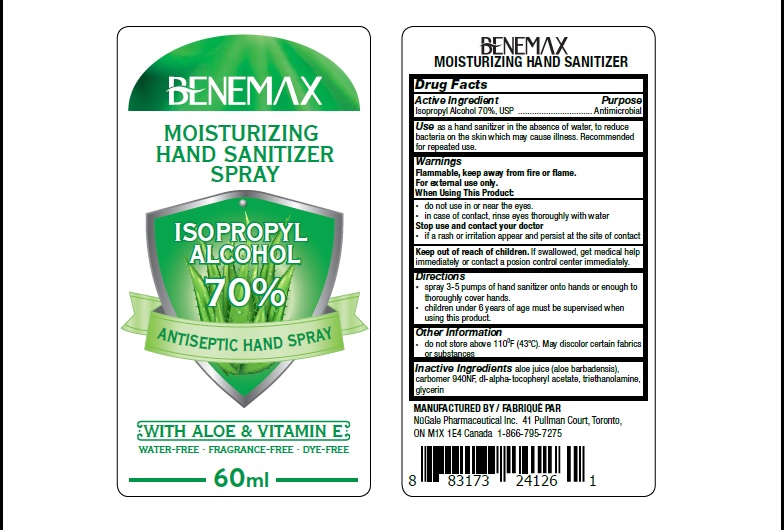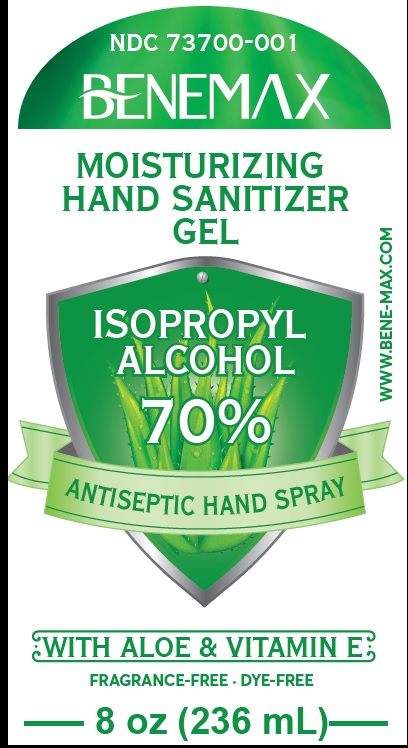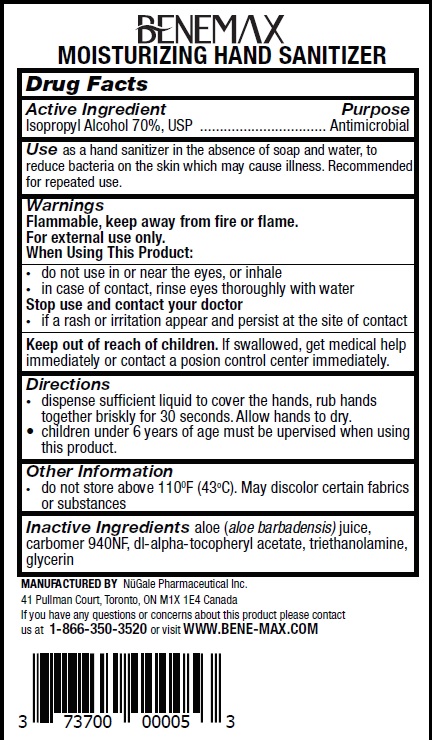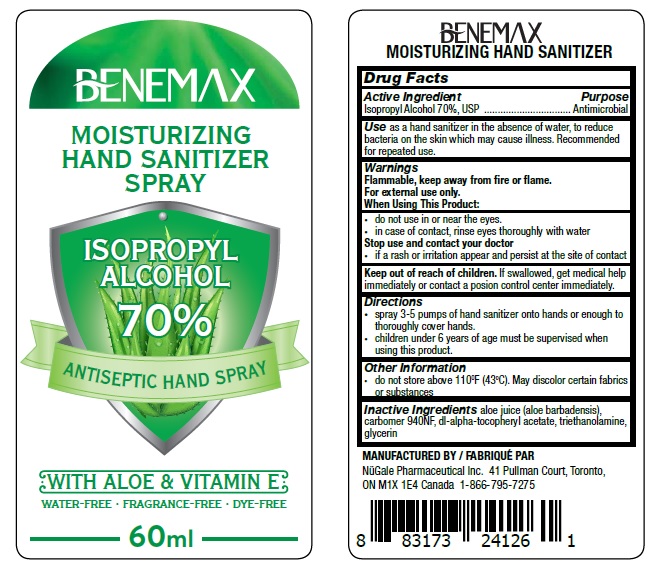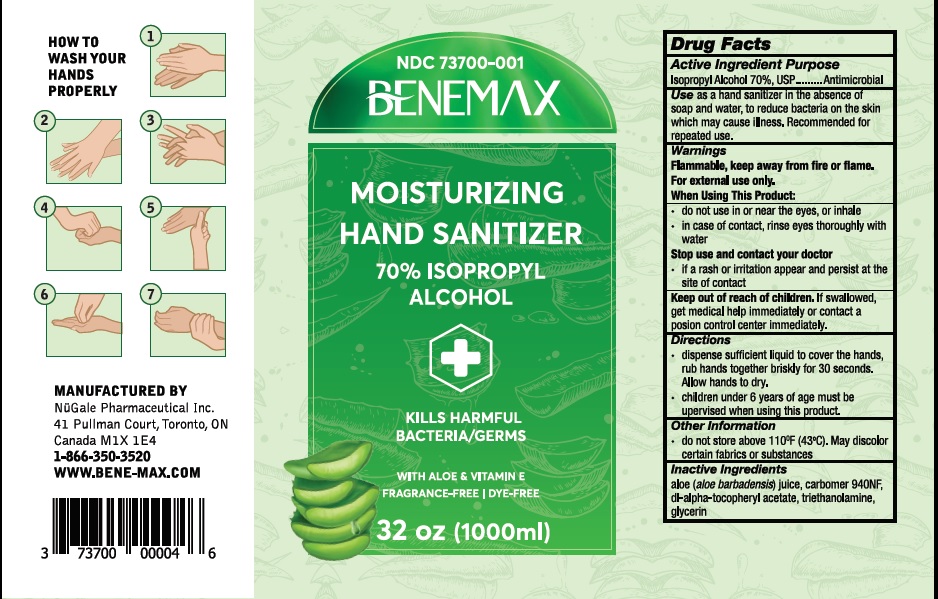 DRUG LABEL: BENEMAX
NDC: 73700-001 | Form: LIQUID
Manufacturer: Nugale Pharmaceutical Inc
Category: otc | Type: HUMAN OTC DRUG LABEL
Date: 20211129

ACTIVE INGREDIENTS: ISOPROPYL ALCOHOL 70 mL/100 mL
INACTIVE INGREDIENTS: ALOE; CARBOMER HOMOPOLYMER TYPE C (ALLYL PENTAERYTHRITOL CROSSLINKED); .ALPHA.-TOCOPHEROL ACETATE, DL-; TROLAMINE; GLYCERIN

Drug Facts

Active ingredient

Isopropyl alcohol 70%, USP

Purpose

Antimicrobial

Uses

as a hand sanitizer when there is no water, to reduce bacteria on the skin which can cause illness. Recommended for repeated use.

Warnings

Flammable, keep away from fire or flame

For external use only

When using this product

- do not use in or near the eyes
- in case of contact, rinse eyes thoroughly with water

Stop use and cantact your doctor

if a rash on irritation appear and remain at the site of contact

Keep out of reach of children.

If swallowed, get medical help right away or contact a Poison Control Center immediately.

Directions

- spray 3·5 pumps of hand sanitizer onto hands or enough to thoroughly cover hands.
- children under 6 years of age must be supervised when using this product.

Other information

- do not store above 110^0F (43^0C). May discolor certain fabrics or substances

Inactive ingredient

aloe juice (aloe barbadensis), carbomer 940NF, di-alpha-tocopheryl acetate, triethanolamine, glycerin